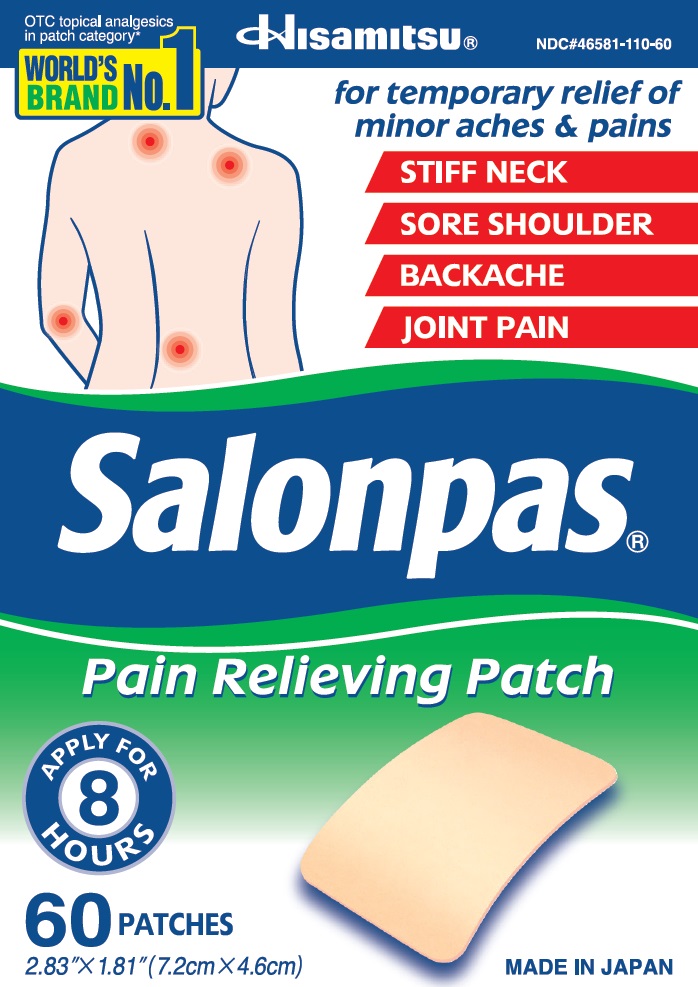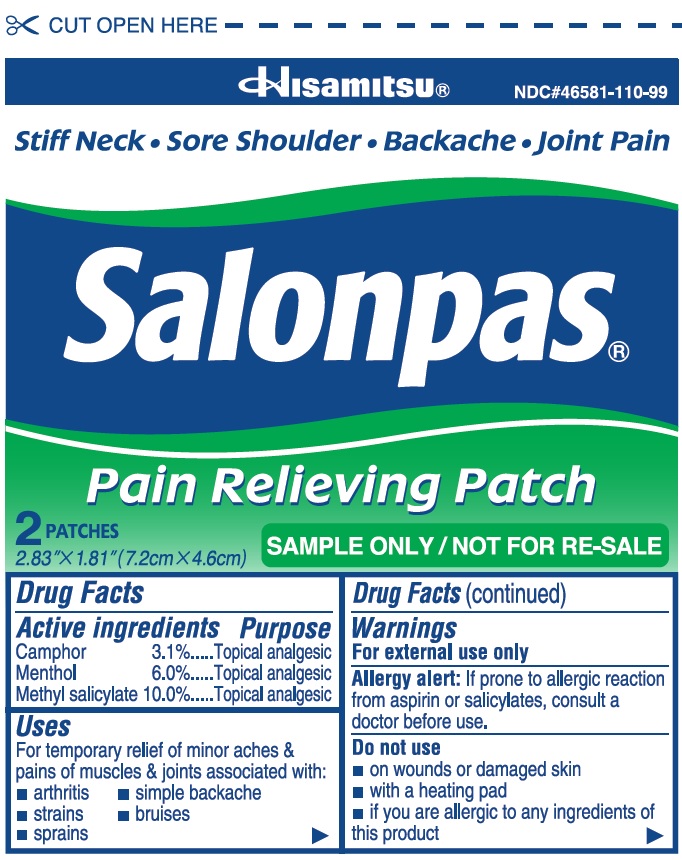 DRUG LABEL: Salonpas
NDC: 46581-110 | Form: PATCH
Manufacturer: Hisamitsu Pharmaceutical Co., Inc.
Category: otc | Type: HUMAN OTC DRUG LABEL
Date: 20241203

ACTIVE INGREDIENTS: CAMPHOR (SYNTHETIC) 21.56 mg/1 1; MENTHOL 41.73 mg/1 1; METHYL SALICYLATE 69.55 mg/1 1
INACTIVE INGREDIENTS: MINERAL OIL; ALUMINUM SILICATE; TITANIUM DIOXIDE

Active ingredients

Camphor 3.1%

Menthol 6.0%

Methyl salicylate 10.0%

Purpose

Topical analgesic

Uses

For temporary relief of minor aches and pains of muscles and joints associated with:

- arthritis
- simple backache
- strains
- bruises
- sprains

Warnings

For external use only

Allergy alert:

If prone to allergic reaction from aspirin or salicylates, consult a doctor before use.

Do not use

- on wounds or damaged skin
- with a heating pad
- if you are allergic to any ingredients of this product

When using this product

- use only as directed
- avoid contact with the eyes, mucous membranes or rashes
- do not bandage tightly

Stop use and ask a doctor if

- rash, itching or excessive skin irritation develops
- conditions worsen
- symptoms persist for more than 7 days
- symptoms clear up and occur again within a few days

If pregnant or breast-feeding,

ask a health professional before use.

Keep out of reach of children.

If swallowed, get medical help or contact a Poison Control Center right away.

Directions

Adults and children 12 years of age and over:

- clean and dry affected area
- remove patch from film
- apply to affected area not more than 3 to 4 times daily
- remove patch from the skin after at most 8-hour application

Children under 12 years of age: consult a doctor

Other information

- avoid storing product in direct sunlight
- protect product from excessive moisture

Inactive ingredients

mineral oil, perfume, polyisobutylene, styrene-isoprene-styrene block copolymer, synthetic aluminum silicate, terpene resin, titanium dioxide

Questions or comments?

Toll free 1-800-826-8861 www.salonpas.us

Principal Display Panel

OTC topical analgesics in patch category*
WORLD'S BRAND NO.1
Hisamitsu NDC#46581-110-60
for temporary relief of minor aches and pains
STIFF NECK
SORE SHOULDER
BACKACHE
JOINT PAIN
Salonpas
Pain Relieving Patch
APPLY FOR 8 HOURS
60 PATCHES
2.83" X 1.81" (7.2cm X 4.6cm)
MADE IN JAPAN

Principal Display Panel

CUT OPEN HERE
Hisamitsu NDC#46581-110-99
Stiff Neck Sore Shoulder Backache Joint Pain
Salonpas
Pain Relieving Patch
2 PATCHES
2.83" X 1.81" (7.2cm X 4.6cm)
SAMPLE ONLY / NOT FOR RE-SALE